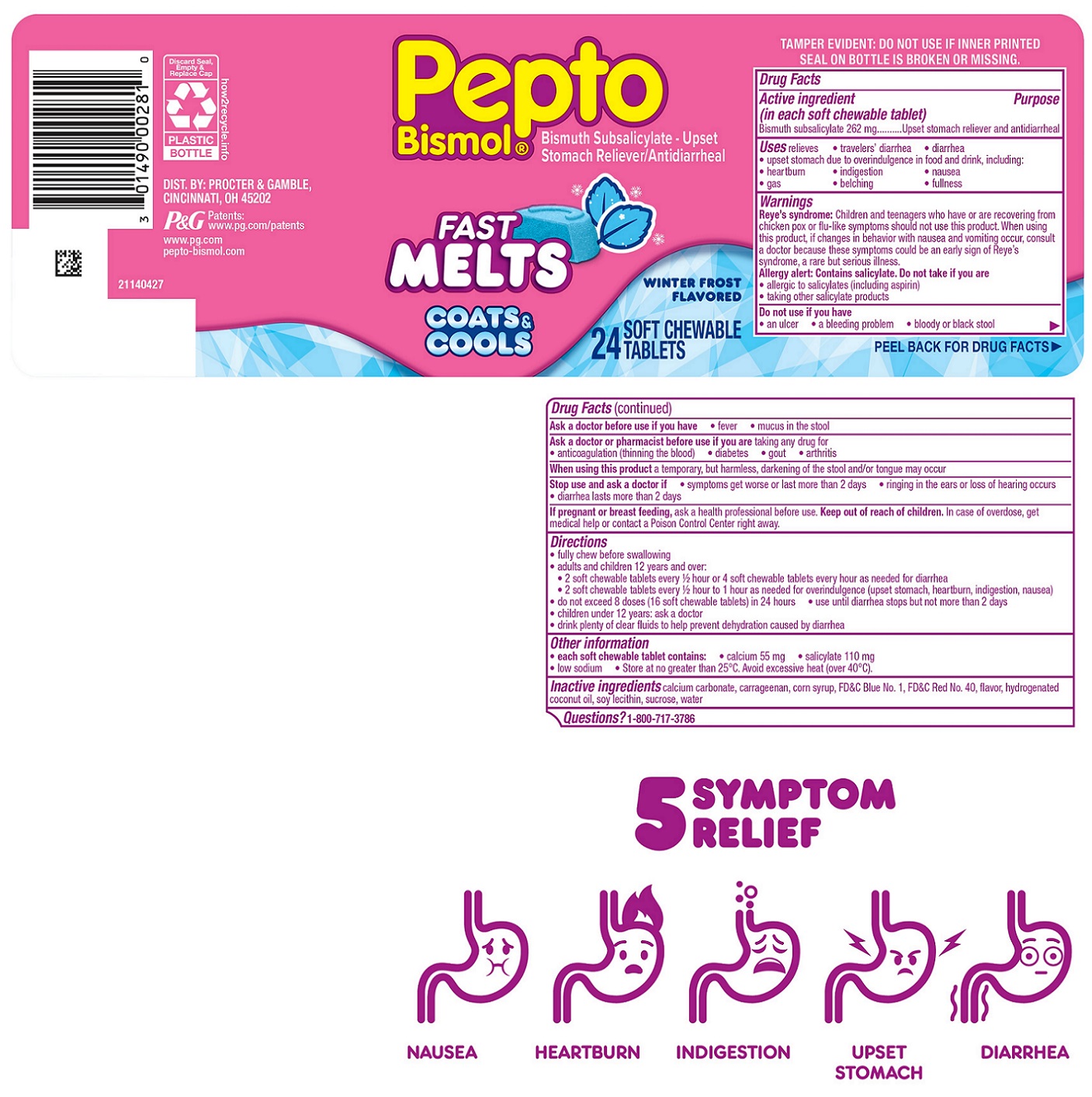 DRUG LABEL: Pepto Bismol Fast Melts
NDC: 69423-832 | Form: TABLET, CHEWABLE
Manufacturer: The Procter & Gamble Manufacturing Company
Category: otc | Type: HUMAN OTC DRUG LABEL
Date: 20251003

ACTIVE INGREDIENTS: BISMUTH SUBSALICYLATE 262 mg/1 1
INACTIVE INGREDIENTS: CARRAGEENAN; CORN SYRUP; FD&C BLUE NO. 1; FD&C RED NO. 40; HYDROGENATED COCONUT OIL; LECITHIN, SOYBEAN; SUCROSE; WATER; CALCIUM CARBONATE

Pepto Bismol Fast Melts Winter Frost Flavored

Drug Facts

Active ingredient (in each soft chewable tablet)

Bismuth subsalicylate 262 mg

Purpose

Upset stomach reliever and antidiarrheal

Uses

relieves

- travelers' diarrhea
- diarrhea
- upset stomach due to overindulgence in food and drink, including:
  - heartburn
  - indigestion
  - nausea
  - gas
  - belching
  - fullness

Warnings

Reye's syndrome: Children and teenagers who have or are recovering from chicken pox or flu-like symptoms should not use this product. When using this product, if changes in behavior with nausea and vomiting occur, consult a doctor because these symptoms could be an early sign of Reye's syndrome, a rare but serious illness.

Allergy alert: Contains salicylate. Do not take if you are
• allergic to salicylates (including aspirin)

• taking other salicylate products

Do not use if

you have

- an ulcer
- a bleeding problem
- bloody or black stool

Ask a doctor before use if you have

- fever
- mucus in the stool

Ask a doctor or pharmacist before use if you are

taking any drug for

- anticoagulation (thinning the blood)
- diabetes
- gout
- arthritis

When using this product

a temporary, but harmless, darkening of the stool and/or tongue may occur

Stop use and ask a doctor if

- symptoms get worse or last more than 2 days
- ringing in the ears or loss of hearing occurs
- diarrhea lasts more than 2 days

PREGNANCY OR BREAST FEEDING

If pregnant or breast feeding, ask a health professional before use.

Keep out of reach of children.

OVERDOSAGE

In case of overdose, get medical help or contact a Poison Control Center right away.

Directions

- fully chew before swallowing
- adults and children 12 years and over:

• 2 soft chewable tablets every 1/2 hour or 4 soft chewable tablets every hour as needed for diarrhea

• 2 soft chewable tablets every 1/2 hour to 1 hour as needed for overindulgence (upset stomach, heartburn, indigestion, nausea)

- do not exceed 8 doses (16 soft chewable tablets) in 24 hours • use until diarrhea stops but not more than 2 days
- children under 12 years: ask a doctor
- drink plenty of clear fluids to help prevent dehydration caused by diarrhea

Other information

- each soft chewable tablet contains: • calcium 55 mg • salicylate 100 mg • low sodium
- Store at no greater than 25°C. Avoid excessive heat (over 40°C).

Inactive ingredients

calcium carbonate, carrageenan, corn syrup, FD&C Blue No. 1, FD&C Red No. 40, flavor, hydrogenated coconut oil, soy lecithin, sucrose, water

Questions?

1-800-717-3786

TAMPER EVIDENT: DO NOT USE IF INNER PRINTED SEAL ON BOTTLE IS BROKEN OR MISSING.

DIST. BY: PROCTER & GAMBLE,

CINCINNATI, OH 45202

PRINCIPAL DISPLAY PANEL - 24 SOFT CHEWABLE TABLETS

Pepto Bismol®

Bismuth Subsalicylate

Upset Stomach Reliever/Antidiarrheal

FAST MELTS

COATS & COOLS

WINTER FROST FLAVORED

24 SOFT CHEWABLE TABLETS